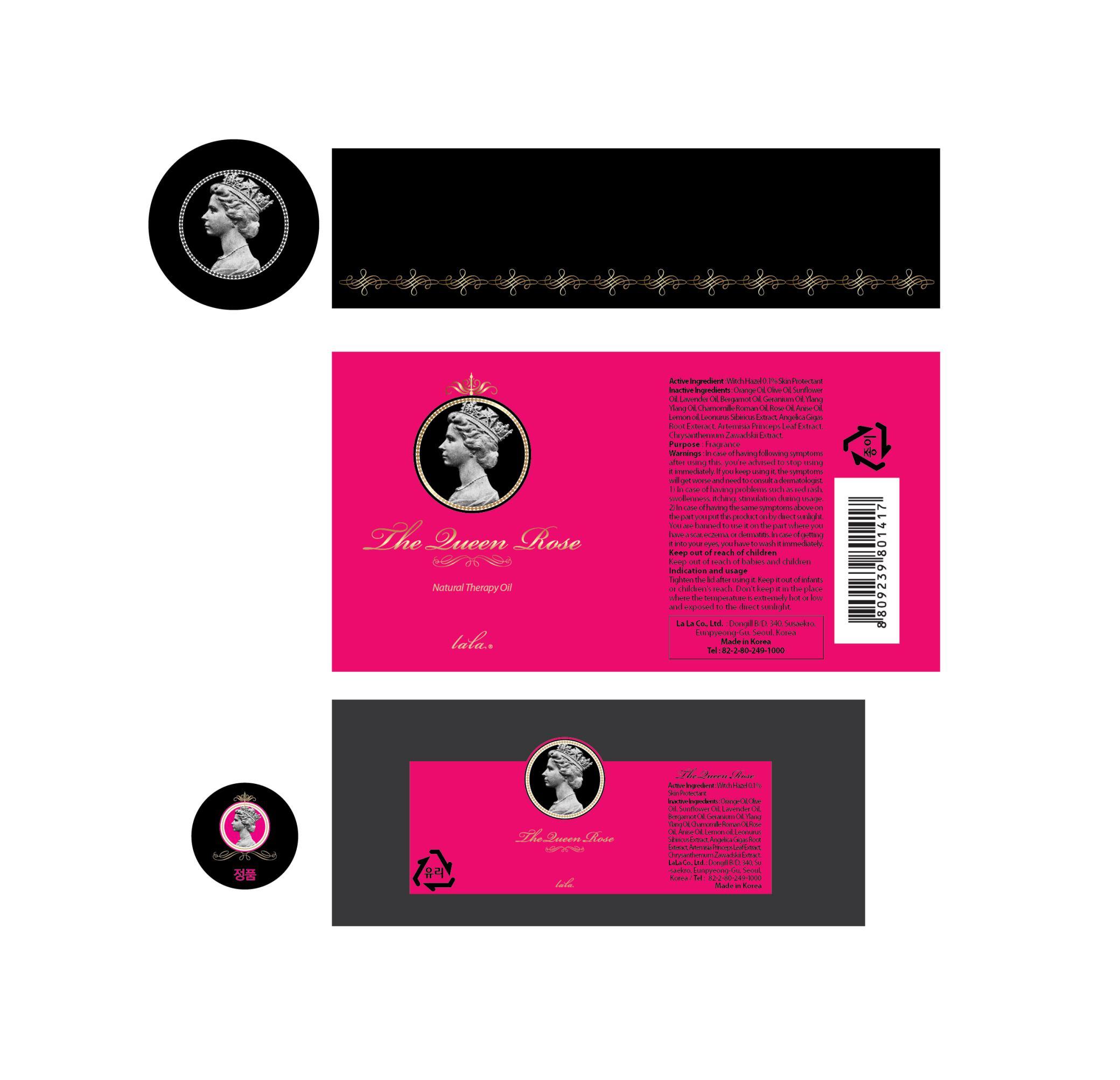 DRUG LABEL: THE QUEEN ROSE
NDC: 55885-010 | Form: LIQUID
Manufacturer: LaLa Co., Ltd.
Category: otc | Type: HUMAN OTC DRUG LABEL
Date: 20130220

ACTIVE INGREDIENTS: WITCH HAZEL 0.005 mg/5 mL
INACTIVE INGREDIENTS: ANISE OIL; BERGAMOT OIL; GERANIUM OIL, ALGERIAN TYPE

ACTIVE INGREDIENT

Active ingredient: Witch Hazel 0.1%

INACTIVE INGREDIENT

Inactive ingredients:
ANISE OIL, BERGAMOT OIL, CHAMOMILLE ROMAN OIL, GERANIUM OIL, LAVENDER OIL, LEMON OIL, ORANGE OIL, OLIVE OIL, ROSE BULGARIA OIL, YLANG YLANG OIL, SUN FLOWER OIL, LEONURUS SIBIRICUS EXTRACT, ANGELICA GIGAS ROOT EXTRACT, ARTEMISIA PRINCEPS LEAF EXTRACT, CHRYSANTHEMUM ZAWADSKII EXTRACT

PURPOSE

Purpose: Skin Protectant, Fragrance

WARNINGS

In case of having following symptoms after using this, you're advised to stop using it immediately.
If you keep using it, the symptoms will get worse and need to consult a dermatologist.
1) In case of having problems such as red rash, swollenness, itching, stimulation during usage.
2) In case of having the same symptoms above on the part you put this product on by direct sunlight.
You are banned to use it on the part where you have a scar, eczema, or dermatitis.
In case of getting it into your eyes, you have to wash it immediately.

KEEP OUT OF REACH OF CHILDREN

Keep out of reach of babies and children.

INDICATIONS AND USAGE

Indication and usage:
Tighten the lid after using it.
Keep it out of infants or children's reach.
Don't keep it in the place where the temperature is extremely hot or low and exposed to the direct sunlight.

DOSAGE AND ADMINISTRATION

Tighten the lid after using it.
Keep it out of infants or children's reach.
Don't keep it in the place where the temperature is extremely hot or low and exposed to the direct sunlight.